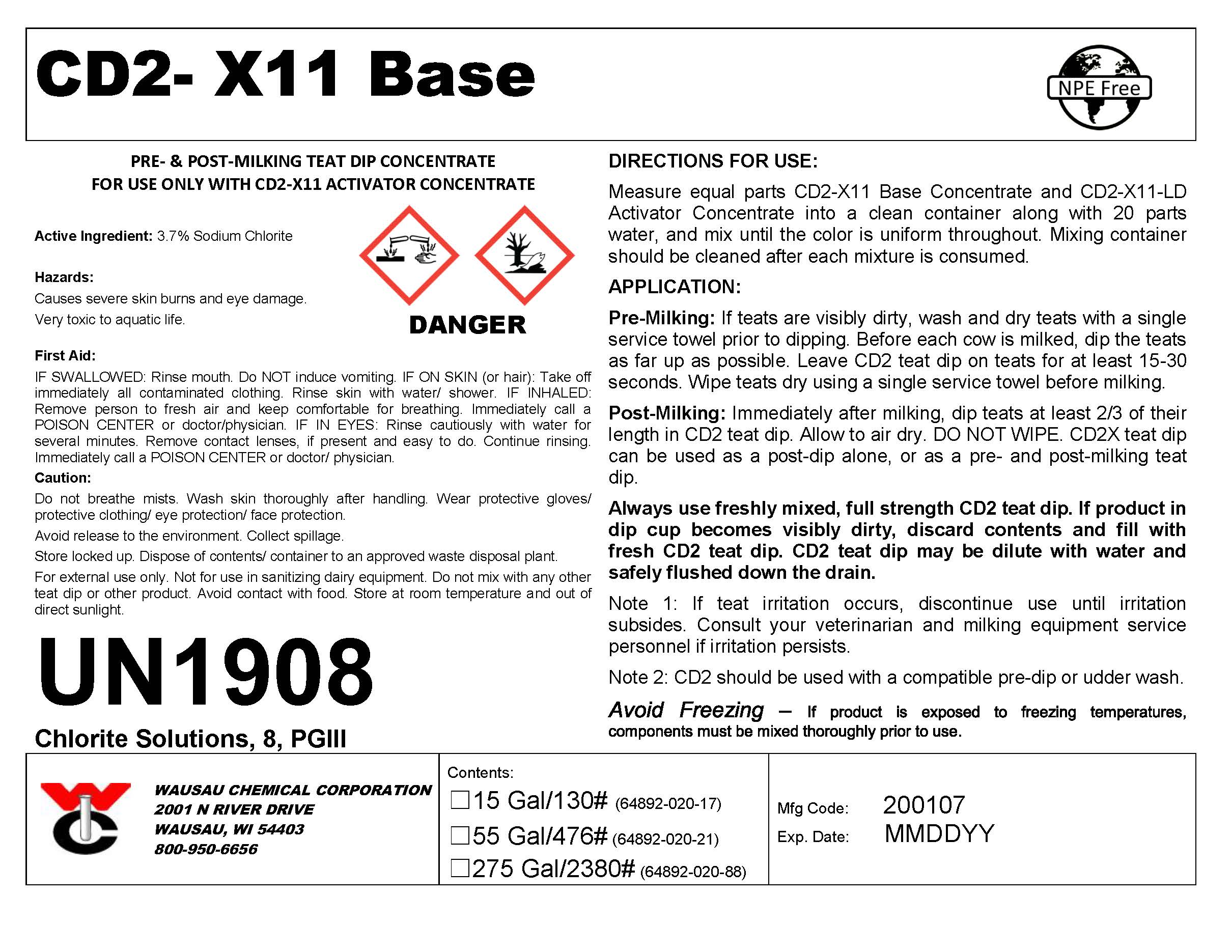 DRUG LABEL: CD2-X11 Base
NDC: 64892-020 | Form: SPRAY, METERED
Manufacturer: Wausau Chemical
Category: animal | Type: OTC ANIMAL DRUG LABEL
Date: 20200107

ACTIVE INGREDIENTS: Sodium Chlorite 38.1 g/1 L

Disposal:

Dispose of contents/container to an approved waste disposal plant.

Hazards/Precautions:

Causes severe skin burns and eye damage.

Very toxic to aquatic life.

Do not breathe mists.

Wash skin thoroughly after handling.

Wear protective gloves/ protective clothing/ eye protection/ face protection.

First Aid:

IF SWALLOWED: Rinse mouth. Do NOT induce vomiting.

IF ON SKIN (or hair): Take immediately all contaminated clothing. Rinse skin with water/ shower.

IF INHALED: Remove person to fresh air and keep comfortable for breathing. Immediately call a POISON CENTER or doctor/physician.

IF IN EYES: Rinse cautiously with water for several minutes. Remove contact lenses, if present and easy to do. Continue rinsing. Immediately call a POISON CENTER or doctor/physician.

Handling Instructions:

For external use only. Not for use in sanitizing dairy equipment. Avoid contact with eyes. Avoid contact with food.

Storage & Handling:

Do not mix with any other teat dip or other product. Store at room temperature and out of direct sunlight.

Avoid freezing - If product is exposed to freezing temperatures, components must be mixed thoroughly prior to use.

Store locked up.

Avoid release to the environment.

DIRECTIONS:

Measure equal volumes of CD2-X11 Base and CD2-X11-LD Activator into a clean container along with 20 parts water, and mix until the color is uniform throughout. Mixing container should be cleaned after each mixture is consumed.

APPLICATION:

Pre-Milking: If teats are visibly dirty, wash and dry teats with a single service towel prior to dipping. Before each cow is milked, dip the teats as far up as possible. Leave CD2 teat dip on teats for at least 15-30 seconds. Wipe teats dry using a single service towel before milking.

Post-Milking: Immediately after milking, dip teats at least 2/3 of their length in CD2 teat dip. Allow to air dry. DO NOT WIPE. CD2 teat dip can be used as a post-dip alone, or as a pre- and post-milking teat dip.

Always use freshly mixed, full strength CD2 teat dip. If product in dip cup becomes visibly dirty, discard contents and fill with fresh CD2 teat dip. CD2 teat dip may be diluted with water and safely flushed down the drain.

Note 1: If teat irritation occurs, discontinue use until irritation subsides. Consult your veterinarian and milking equipment service personnel if irritation persists.

Note 2: CD2 should be used with a compatible pre-dip or udder wash.

Active Ingredient:
Sodium Chlorite.....................................................................................3.7%

Wausau Chemical Corporation

2001 N River Drive

Wausau, WI 54403

800-950-6656